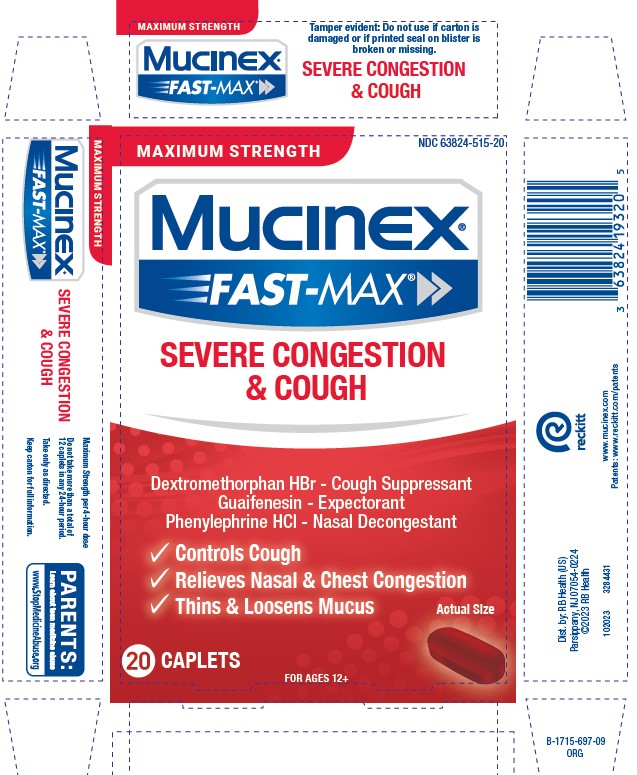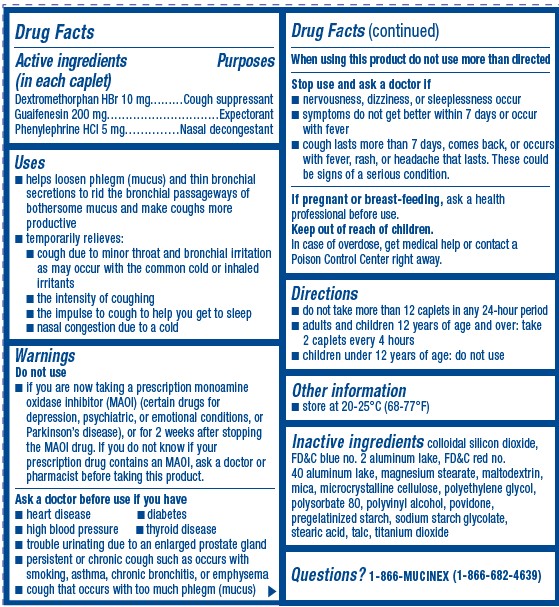 DRUG LABEL: Mucinex Fast-Max
NDC: 63824-515 | Form: TABLET, FILM COATED
Manufacturer: RB Health (US) LLC
Category: otc | Type: HUMAN OTC DRUG LABEL
Date: 20231201

ACTIVE INGREDIENTS: GUAIFENESIN 200 mg/1 1; PHENYLEPHRINE HYDROCHLORIDE 5 mg/1 1; DEXTROMETHORPHAN HYDROBROMIDE 10 mg/1 1
INACTIVE INGREDIENTS: STARCH, CORN; FD&C BLUE NO. 2; FD&C RED NO. 40; MAGNESIUM STEARATE; MALTODEXTRIN; MICA; MICROCRYSTALLINE CELLULOSE; POLYETHYLENE GLYCOL, UNSPECIFIED; POLYSORBATE 80; POLYVINYL ALCOHOL, UNSPECIFIED; POVIDONE, UNSPECIFIED; SILICON DIOXIDE; SODIUM STARCH GLYCOLATE TYPE A POTATO; STEARIC ACID; TALC; TITANIUM DIOXIDE

Mucinex® Fast-Max®
Severe Congestion & Cough

Drug Facts

ACTIVE INGREDIENT

PURPOSE

Active ingredients (in each caplet) | Purposes
Dextromethorphan HBr 10 mg | Cough suppressant
Guaifenesin 200 mg | Expectorant
Phenylephrine HCl 5 mg | Nasal decongestant

Uses

- helps loosen phlegm (mucus) and thin bronchial secretions to rid the bronchial passageways of bothersome mucus and make coughs more productive
- temporarily relieves:
  - cough due to minor throat and bronchial irritation as may occur with the common cold or inhaled irritants
  - the intensity of coughing
  - the impulse to cough to help you get to sleep
  - nasal congestion due to a cold

Warnings

Do not use

- if you are now taking a prescription monoamine oxidase inhibitor (MAOI) (certain drugs for depression, psychiatric, or emotional conditions, or Parkinson's disease), or for 2 weeks after stopping the MAOI drug. If you do not know if your prescription drug contains an MAOI, ask a doctor or pharmacist before taking this product.

Ask a doctor before use if you have

- heart disease
- diabetes
- high blood pressure
- thyroid disease
- trouble urinating due to an enlarged prostate gland
- persistent or chronic cough such as occurs with smoking, asthma, chronic bronchitis, or emphysema
- cough that occurs with too much phlegm (mucus)

When using this product do not use more than directed

Stop use and ask a doctor if

- nervousness, dizziness, or sleeplessness occur
- symptoms do not get better within 7 days or occur with fever
- cough comes back, or occurs with fever, rash, or headache that lasts. These could be signs of a serious condition.

PREGNANCY OR BREAST FEEDING

If pregnant or breast-feeding,ask a health professional before use.

Keep out of reach of children.

In case of overdose, get medical help or contact a Poison Control Center right away.

Directions

- do not take more than 12 caplets in any 24-hour period
- adults and children 12 years of age and over: take 2 caplets every 4 hours
- children under 12 years of age: do not use

Other information

- store between 20-25°C (68-77°F)

Inactive ingredients

corn starch, FD&C blue no. 2 aluminum lake, FD&C red no. 40 aluminum lake, magnesium stearate, maltodextrin, mica, microcrystalline cellulose, polyethylene glycol, polysorbate 80, polyvinyl alcohol, povidone, silicon dioxide, sodium starch glycolate, stearic acid, talc, titanium dioxide

Questions?

1-866-MUCINEX (1-866-682-4639)
You may also report side effects to this phone number.

Dist. by: Reckitt Benckiser, Parsippany, NJ 07054-0224

PRINCIPAL DISPLAY PANEL - 20 Caplet Blister Pack Carton

MAXIMUM STRENGTH
NDC 63824-515-01

Mucinex®
FAST-MAX®

SEVERE CONGESTION
& COUGH

Dextromethorphan HBr – Cough Suppressant
Guaifenesin – Expectorant
Phenylephrine HCl – Nasal Decongestant

- Controls Cough
- Relieves Nasal & Chest Congestion
- Thins & Loosens Mucus

20 CAPLETS
FOR AGES 12+